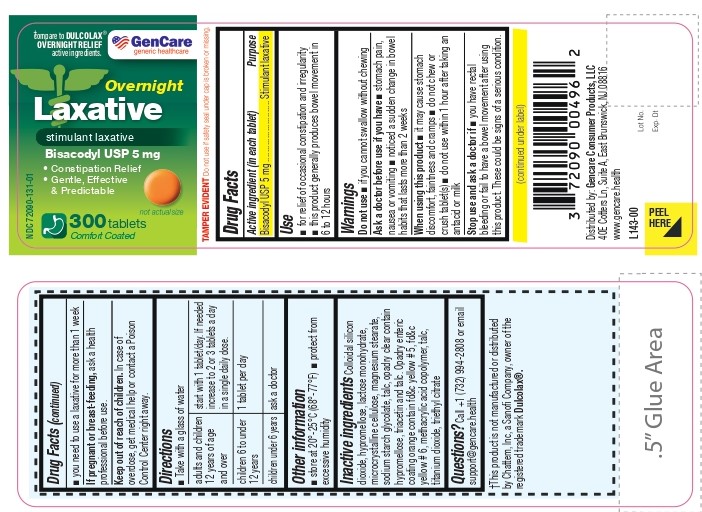 DRUG LABEL: BISACODYL
NDC: 72090-131 | Form: TABLET, COATED
Manufacturer: Pioneer Life Sciences, LLC
Category: otc | Type: HUMAN OTC DRUG LABEL
Date: 20260302

ACTIVE INGREDIENTS: BISACODYL 5 mg/1 1
INACTIVE INGREDIENTS: SILICON DIOXIDE; HYPROMELLOSE, UNSPECIFIED; LACTOSE MONOHYDRATE; MICROCRYSTALLINE CELLULOSE; MAGNESIUM STEARATE; SODIUM STARCH GLYCOLATE TYPE A; talc; TRIACETIN; FD&C YELLOW NO. 5; FD&C YELLOW NO. 6; METHACRYLIC ACID - METHYL METHACRYLATE COPOLYMER (1:1); titanium dioxide; triethyl citrate

Bisacodyl Tablets USP 5 mg

Active ingredient (in each tablet)

Bisacodyl USP 5 mg

Purpose

Stimulant laxative

Use

■ for relief of occasional constipation and irregularity
■ this product generally produces bowel movement in 6 to 12 hours

Warnings

Do not use ■ if you cannot swallow without chewing

Ask a doctor before use if you have ■ stomach pain, nausea or vomiting ■ noticed a sudden change in bowel habits that lasts more than 2 weeks

When using this product

■ it may cause stomach discomfort, faintness and cramps

■ do not chew or crush tablet(s)

■ do not use within 1 hour after taking an antacid or milk

Stop use and ask a doctor if

■ you have rectal bleeding or fail to have a bowel movement after using this product. These could be signs of a serious condition.

■ you need to use a laxative for more than 1 week

PREGNANCY OR BREAST FEEDING

If pregnant or breast-feeding, ask a health professional before use.

Keep out of reach of children. In case of overdose, get medical help or contact a Poison Control Center right away.

Directions

■ Take with a glass of water

adults and children12 years of age and over | start with 1 tablet/day. If needed increase to 2 or 3 tablets a day in a single daily dose.
children 6 to under 12 years | 1 tablet per day
children under 6 years | ask a doctor

Other information

■ store at 20°-25°C (68°-77°F)

■ protect from excessive humidity

Inactive ingredients

Colloidal silicon dioxide, hypromellose, lactose monohydrate, microcrystalline cellulose, magnesium stearate, sodium starch glycolate, talc, opadry clear contain hypromellose, triacetin and talc. Opadry enteric coating orange contain fd&c yellow # 5, fd&c yellow # 6, methacrylic acid copolymer, talc, titanium dioxide, triethyl citrate

Questions?

Call +1 (732) 994-2808 or email support@gencare.health

†This product is not manufactured or distributed by Chattem, Inc, a Sanofi Company, owner of the registered trademark Dulcolax®.